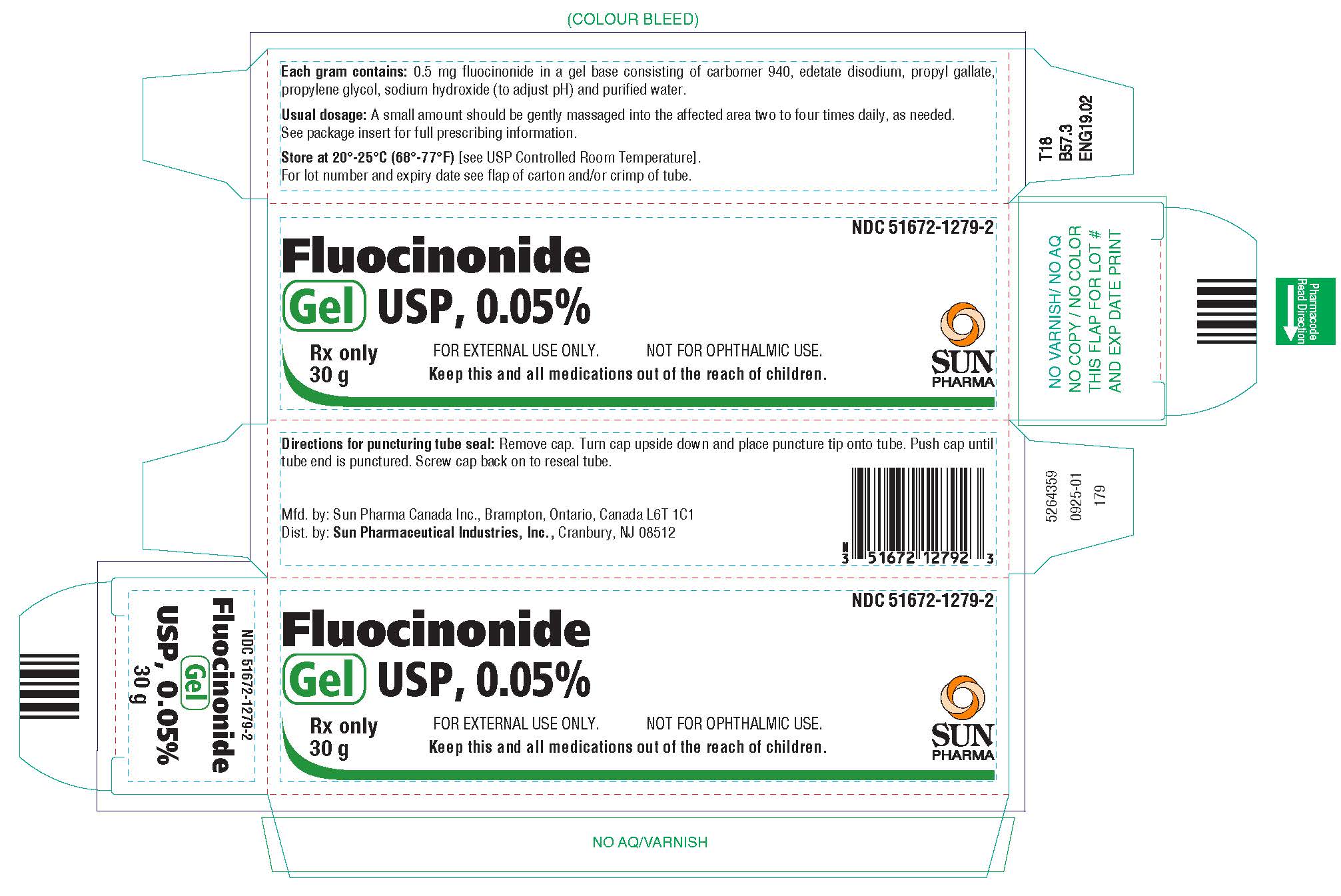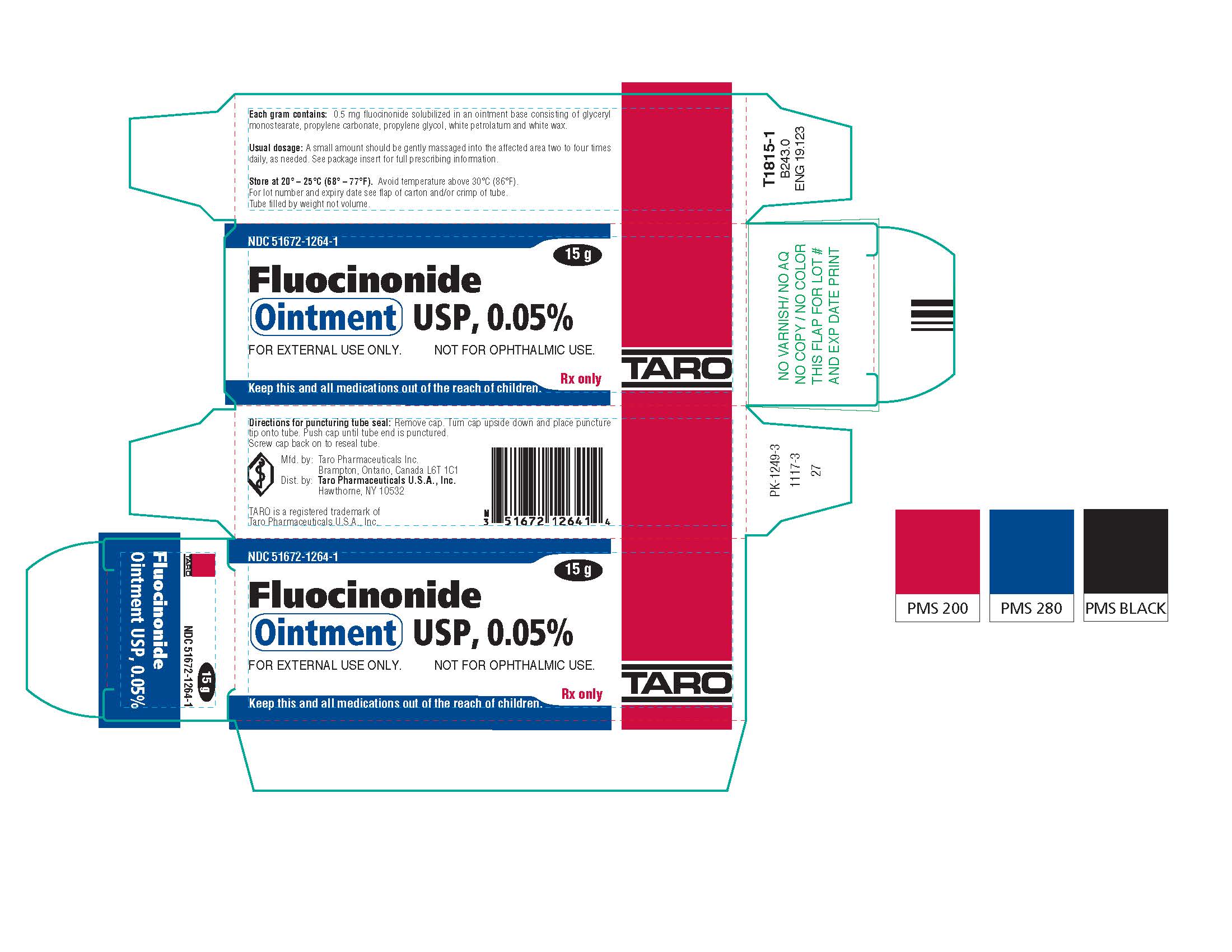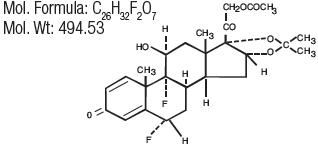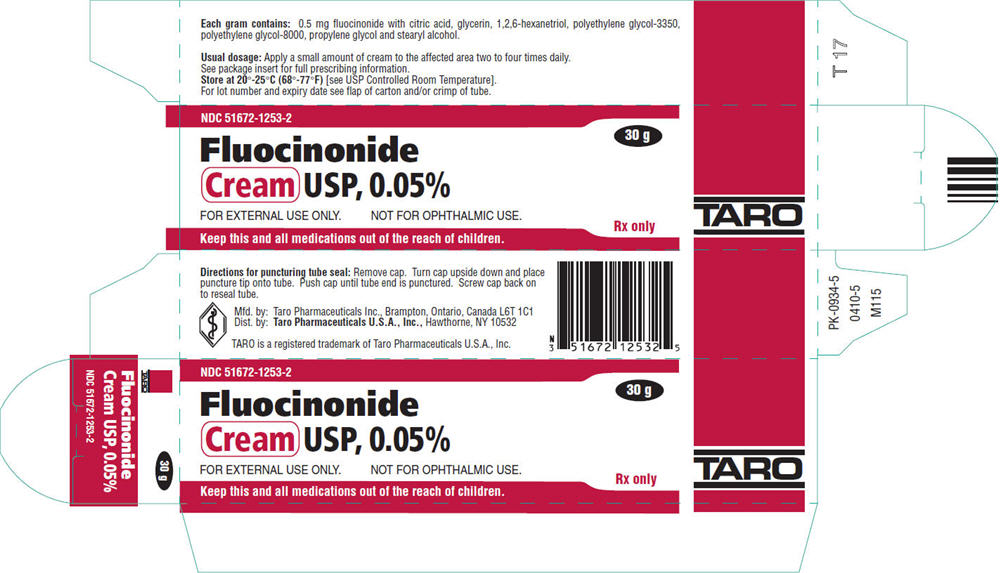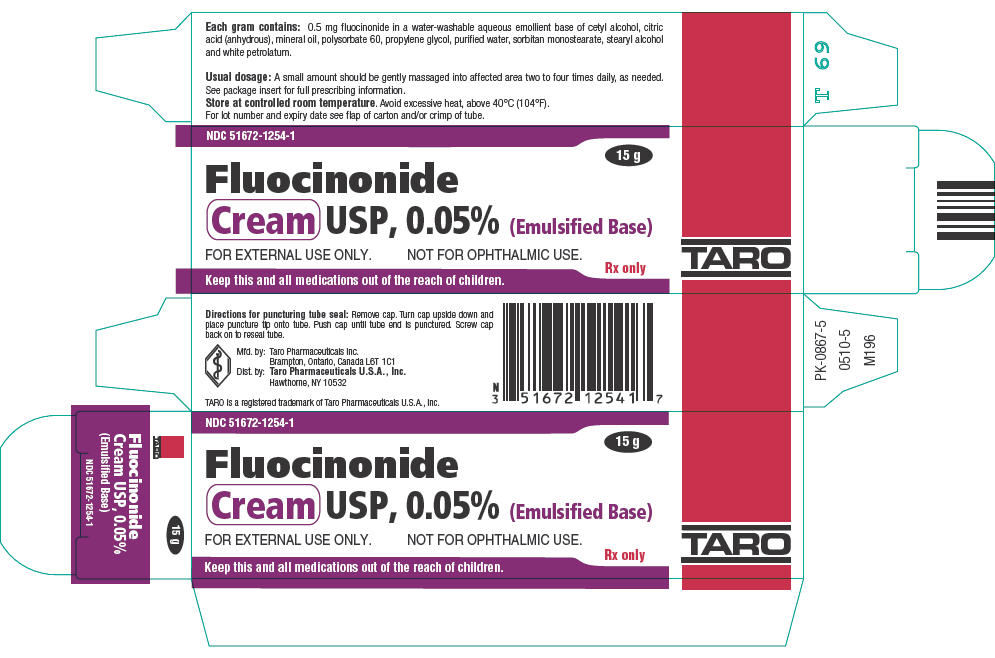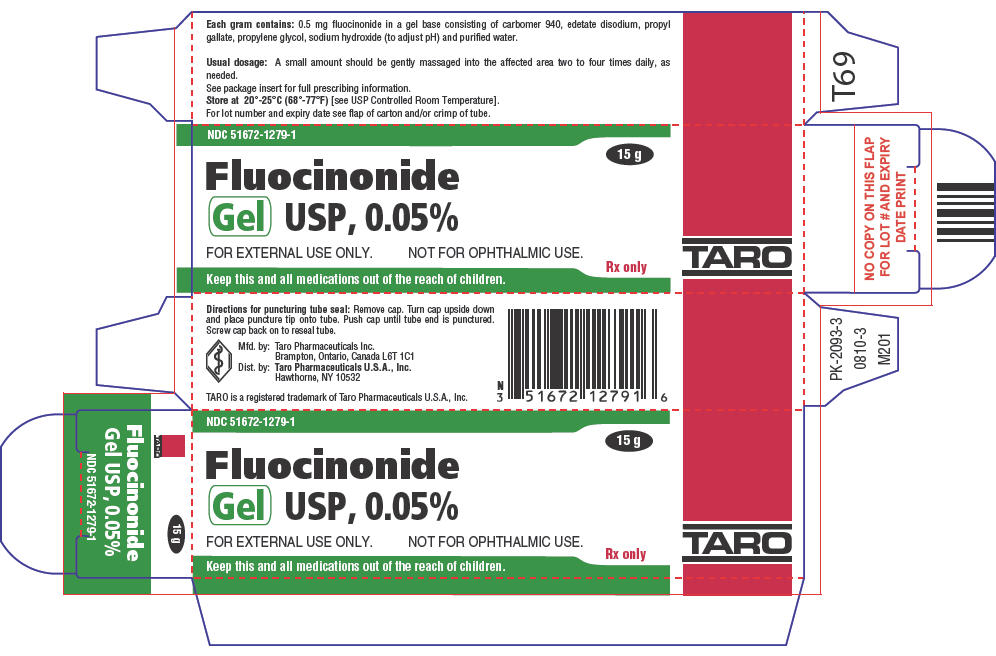 DRUG LABEL: Fluocinonide
NDC: 51672-1253 | Form: CREAM
Manufacturer: Sun Pharmaceutical Industries, Inc.
Category: prescription | Type: HUMAN PRESCRIPTION DRUG LABEL
Date: 20251223

ACTIVE INGREDIENTS: FLUOCINONIDE 0.5 mg/1 g
INACTIVE INGREDIENTS: CITRIC ACID MONOHYDRATE; GLYCERIN; 1,2,6-HEXANETRIOL; POLYETHYLENE GLYCOL 3350; POLYETHYLENE GLYCOL 8000; PROPYLENE GLYCOL; STEARYL ALCOHOL

Fluocinonide Cream USP, 0.05%
Fluocinonide Cream USP, 0.05% (Emulsified Base)
Fluocinonide Gel USP, 0.05%
Fluocinonide Ointment USP, 0.05%

For External Use Only. Not For Ophthalmic Use.

Rx only

DESCRIPTION

Fluocinonide Cream USP, 0.05%, Fluocinonide Cream USP, 0.05% (Emulsified Base), Fluocinonide Gel USP, 0.05% and Fluocinonide Ointment USP, 0.05% are intended for topical administration. The active component in each is the corticosteroid fluocinonide, which is the 21-acetate ester of fluocinolone acetonide and has the chemical name pregna-1,4-diene-3,20-dione,21-(acetyloxy)-6,9-difluoro-11-hydroxy-16,17-[(1-methylethylidene)bis(oxy)]-,(6α,11β,16α)-. It has the following chemical structure:

Fluocinonide Cream USP, 0.05% contains fluocinonide 0.5 mg/g in a specially formulated cream base consisting of citric acid, glycerin, 1,2,6-hexanetriol, polyethylene glycol-3350, polyethylene glycol-8000, propylene glycol and stearyl alcohol. This white cream vehicle is greaseless, non-staining, anhydrous and completely water miscible. The base provides emollient and hydrophylic properties.

Fluocinonide Cream USP, 0.05% (Emulsified Base) contains fluocinonide 0.5 mg/g in a water-washable aqueous emollient base of cetyl alcohol, citric acid (anhydrous), mineral oil, polysorbate 60, propylene glycol, purified water, sorbitan monostearate, stearyl alcohol and white petrolatum.

Fluocinonide Gel USP, 0.05% contains fluocinonide 0.5 mg/g in a specially formulated gel base consisting of carbomer 940, edetate disodium, propyl gallate, propylene glycol, sodium hydroxide (to adjust pH) and purified water. This clear, colorless, thixotropic vehicle is greaseless, non-staining and completely water miscible.

Fluocinonide Ointment USP, 0.05% contains fluocinonide 0.5 mg/g in a specially formulated ointment base consisting of glyceryl monostearate, propylene carbonate, propylene glycol, white petrolatum and white wax. It provides the occlusive and emollient effects desirable in an ointment.

In the Fluocinonide Cream USP, 0.05%, Fluocinonide Gel USP, 0.05%, and Fluocinonide Ointment USP, 0.05% formulations, the active ingredient is totally in solution.

CLINICAL PHARMACOLOGY

Topical corticosteroids share anti-inflammatory, anti-pruritic and vasoconstrictive actions.

The mechanism of anti-inflammatory activity of the topical corticosteroids is unclear. Various laboratory methods, including vasoconstrictor assays, are used to compare and predict potencies and/or clinical efficacies of the topical corticosteroids. There is some evidence to suggest that a recognizable correlation exists between vasoconstrictor potency and therapeutic efficacy in man.

Pharmacokinetics

The extent of percutaneous absorption of topical corticosteroids is determined by many factors including the vehicle, the integrity of the epidermal barrier, and the use of occlusive dressings.

Topical corticosteroids can be absorbed from normal intact skin. Inflammation and/or other disease processes in the skin increase percutaneous absorption. Occlusive dressings substantially increase the percutaneous absorption of topical corticosteroids. Thus, occlusive dressings may be a valuable therapeutic adjunct for treatment of resistant dermatoses (see DOSAGE AND ADMINISTRATION).

Once absorbed through the skin, topical corticosteroids are handled through pharmacokinetic pathways similar to systemically administered corticosteroids. Corticosteroids are bound to plasma proteins in varying degrees. Corticosteroids are metabolized primarily in the liver and are then excreted by the kidneys. Some of the topical corticosteroids and their metabolites are also excreted into the bile.

INDICATIONS AND USAGE

Fluocinonide Cream USP, 0.05%, Fluocinonide Cream USP, 0.05% (Emulsified Base), Fluocinonide Gel USP, 0.05% and Fluocinonide Ointment USP, 0.05% are indicated for the relief of the inflammatory and pruritic manifestations of corticosteroid-responsive dermatoses.

CONTRAINDICATIONS

Topical corticosteroids are contraindicated in those patients with a history of hypersensitivity to any of the components of the preparations.

PRECAUTIONS

General

Systemic absorption of topical corticosteroids has produced reversible hypothalamic-pituitary-adrenal (HPA) axis suppression, manifestations of Cushing's syndrome, hyperglycemia, and glucosuria in some patients.

Conditions which augment systemic absorption include the application of the more potent steroids, use over large surface areas, prolonged use, and the addition of occlusive dressings.

Therefore, patients receiving a large dose of a potent topical steroid applied to a large surface area or under an occlusive dressing should be evaluated periodically for evidence of HPA axis suppression by using the urinary free cortisol and ACTH stimulation tests. If HPA axis suppression is noted, an attempt should be made to withdraw the drug, to reduce the frequency of application, or to substitute a less potent steroid.

Recovery of HPA axis function is generally prompt and complete upon discontinuation of the drug. Infrequently, signs and symptoms of steroid withdrawal may occur, requiring supplemental systemic corticosteroids.

Children may absorb proportionally larger amounts of topical corticosteroids and thus be more susceptible to systemic toxicity (see PRECAUTIONS - Pediatric Use). If irritation develops, topical corticosteroids should be discontinued and appropriate therapy instituted.

As with any topical corticosteroid product, prolonged use may produce atrophy of the skin and subcutaneous tissues. When used on intertriginous or flexor areas, or on the face, this may occur even with short-term use.

In the presence of dermatological infections, the use of an appropriate antifungal or antibacterial agent should be instituted. If a favorable response does not occur promptly, the corticosteroid should be discontinued until the infection has been adequately controlled.

Information for the Patient

Patients using topical corticosteroids should receive the following information and instructions:

1. This medication is to be used as directed by the physician. It is for external use only. Avoid contact with the eyes.
2. Patients should be advised not to use this medication for any disorder other than for which it was prescribed.
3. The treated skin area should not be bandaged or otherwise covered or wrapped as to be occlusive unless directed by the physician.
4. Patients should report any signs of local adverse reactions, especially under occlusive dressing.
5. Parents of pediatric patients should be advised not to use tight-fitting diapers or plastic pants on a child being treated in the diaper area, as these garments may constitute occlusive dressings.

Laboratory Tests

The following tests may be helpful in evaluating the HPA axis suppression:

- Urinary free cortisol test
- ACTH stimulation test

Carcinogenesis, Mutagenesis, and Impairment of Fertility

Long-term animal studies have not been performed to evaluate the carcinogenic potential or the effect on fertility of topical corticosteroids.

Studies to determine mutagenicity with prednisolone and hydrocortisone have revealed negative results.

Pregnancy Category C

TERATOGENIC EFFECTS

Corticosteroids are generally teratogenic in laboratory animals when administered systemically at relatively low dosage levels. The more potent corticosteroids have been shown to be teratogenic after dermal application in laboratory animals. There are no adequate and well-controlled studies in pregnant women on teratogenic effects from topically applied corticosteroids. Therefore, topical corticosteroids should be used during pregnancy only if the potential benefit justifies the potential risk to the fetus. Drugs of this class should not be used extensively on pregnant patients, in large amounts, or for prolonged periods of time.

Nursing Mothers

It is not known whether topical administration of corticosteroids could result in sufficient systemic absorption to produce detectable quantities in breast milk. Systemically administered corticosteroids are secreted into breast milk in quantities notlikely to have a deleterious effect on the infant. Nevertheless, caution should be exercised when topical corticosteroids are administered to a nursing woman.

Pediatric Use

Pediatric patients may demonstrate greater susceptibility to topical corticosteroid-induced hypothalamic-pituitary-adrenal (HPA) axis suppression and Cushing's syndrome than mature patients because of a larger skin surface area to body weight ratio.

HPA axis suppression, Cushing's syndrome, and intracranial hypertension have been reported in children receiving topical corticosteroids. Manifestations of adrenal suppression in children include linear growth retardation, delayed weight gain, low plasma cortisol levels, and absence of response to ACTH stimulation. Manifestations of intracranial hypertension include bulging fontanelles, headaches, and bilateral papilledema.

Administration of topical corticosteroids to children should be limited to the least amount compatible with an effective therapeutic regimen. Chronic corticosteroid therapy may interfere with the growth and development of children.

ADVERSE REACTIONS

The following local adverse reactions are reported infrequently with topical corticosteroids, but may occur more frequently with the use of occlusive dressings. These reactions are listed in an approximate decreasing order of occurrence:

Burning
Itching
Irritation
Dryness
Folliculitis

Hypertrichosis
Acneiform Eruptions
Hypopigmentation
Perioral Dermatitis
Allergic Contact Dermatitis

Maceration of the Skin
Secondary Infection
Skin Atrophy
Striae
Miliaria

To report SUSPECTED ADVERSE REACTIONS, contact Sun Pharmaceutical Industries, Inc., at 1-866-923-4914 or FDA at 1-800-FDA-1088 or www.fda.gov/medwatch.

OVERDOSAGE

Topically applied corticosteroids can be absorbed in sufficient amounts to produce systemic effects (see PRECAUTIONS).

DOSAGE AND ADMINISTRATION

Fluocinonide Cream USP, 0.05%, Fluocinonide Cream USP, 0.05% (Emulsified Base), Fluocinonide Gel USP, 0.05% and Fluocinonide Ointment USP, 0.05% are generally applied to the affected area as a thin film from two to four times daily depending on the severity of the condition.

Occlusive dressings may be used for the management of psoriasis or recalcitrant conditions.

If an infection develops, the use of occlusive dressings should be discontinued and appropriate antimicrobial therapy instituted.

HOW SUPPLIED

STORAGE AND HANDLING

Fluocinonide Cream USP, 0.05% is supplied in 15 g (NDC 51672-1253-1), 30 g (NDC 51672-1253-2), 60 g (NDC 51672-1253-3) and 120 g (NDC 51672-1253-4) tubes.

Store at 20°-25°C (68°-77°F)[see USP Controlled Room Temperature].

Fluocinonide Cream USP, 0.05% (Emulsified Base) is supplied in 15 g (NDC 51672-1254-1), 30 g (NDC 51672-1254-2) and 60 g (NDC 51672-1254-3) tubes.

Store at controlled room temperature.Avoid excessive heat, above 40°C (104°F).

Fluocinonide Gel USP, 0.05% is supplied in 15 g (NDC 51672-1279-1), 30 g (NDC 51672-1279-2) and 60 g (NDC 51672-1279-3) tubes.

Store at 20°- 25°C (68°- 77°F)[see USP Controlled Room Temperature].

Fluocinonide Ointment USP, 0.05% is supplied in 15 g (NDC 51672-1264-1), 30 g (NDC 51672-1264-2) and 60 g (NDC 51672-1264-3) tubes.

Store at 20°-25°C (68°-77°F).Avoid temperature above 30°C (86°F).

Mfd. by: Sun Pharma Canada Inc., Brampton, Ontario, Canada L6T 1C1
Dist. by: Sun Pharmaceutical Industries, Inc.,Cranbury, NJ 08512

Revised: September 2025 5264571-0925-01 77

PRINCIPAL DISPLAY PANEL - 30 g Tube Carton (Cream)

NDC 51672-1253-2

Fluocinonide
Cream USP, 0.05%

FOR EXTERNAL USE ONLY.
NOT FOR OPHTHALMIC USE.

Keep this and all medications out of the reach of children.

30 g

Rx only

TARO

PRINCIPAL DISPLAY PANEL - 15 g Tube Carton

NDC 51672-1254-1

Fluocinonide
Cream USP, 0.05% (Emulsified Base)

FOR EXTERNAL USE ONLY.
NOT FOR OPHTHALMIC USE.

Keep this and all medications out of the reach of children.

15 g

Rx only

TARO

PRINCIPAL DISPLAY PANEL - 15 g Tube Carton

NDC 51672-1279-1

Fluocinonide
Gel USP, 0.05%

FOR EXTERNAL USE ONLY.
NOT FOR OPHTHALMIC USE.

Keep this and all medications out of the reach of children.

15 g

Rx only

TARO

PRINCIPAL DISPLAY PANEL - 15 g Tube Carton

NDC 51672-1264-1

Fluocinonide
Ointment USP, 0.05%